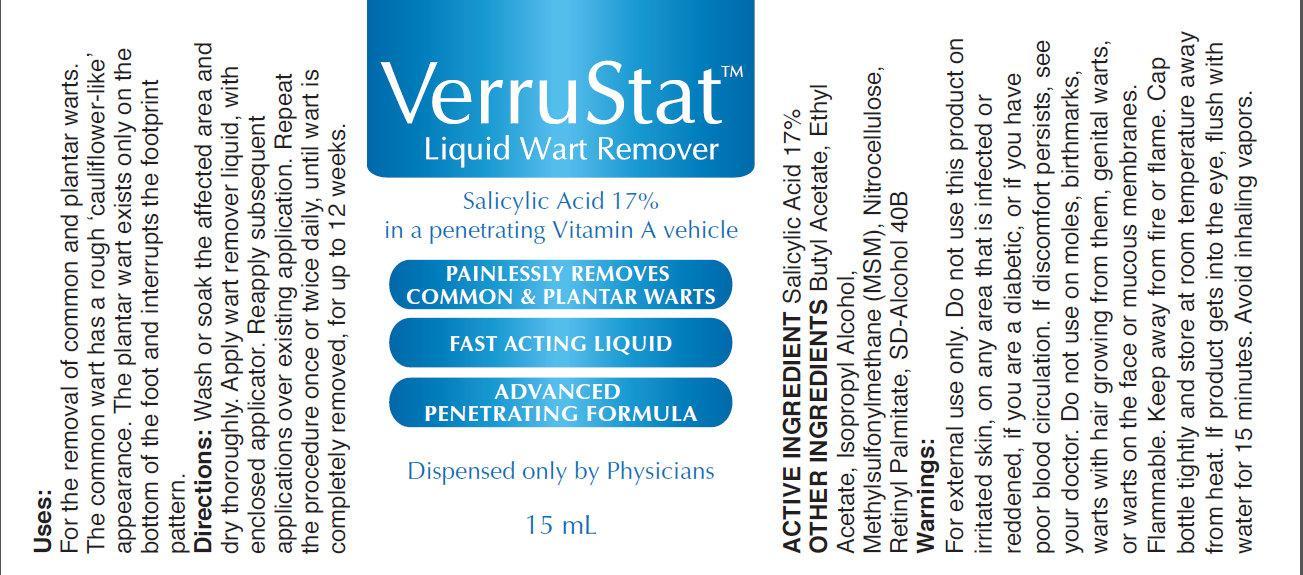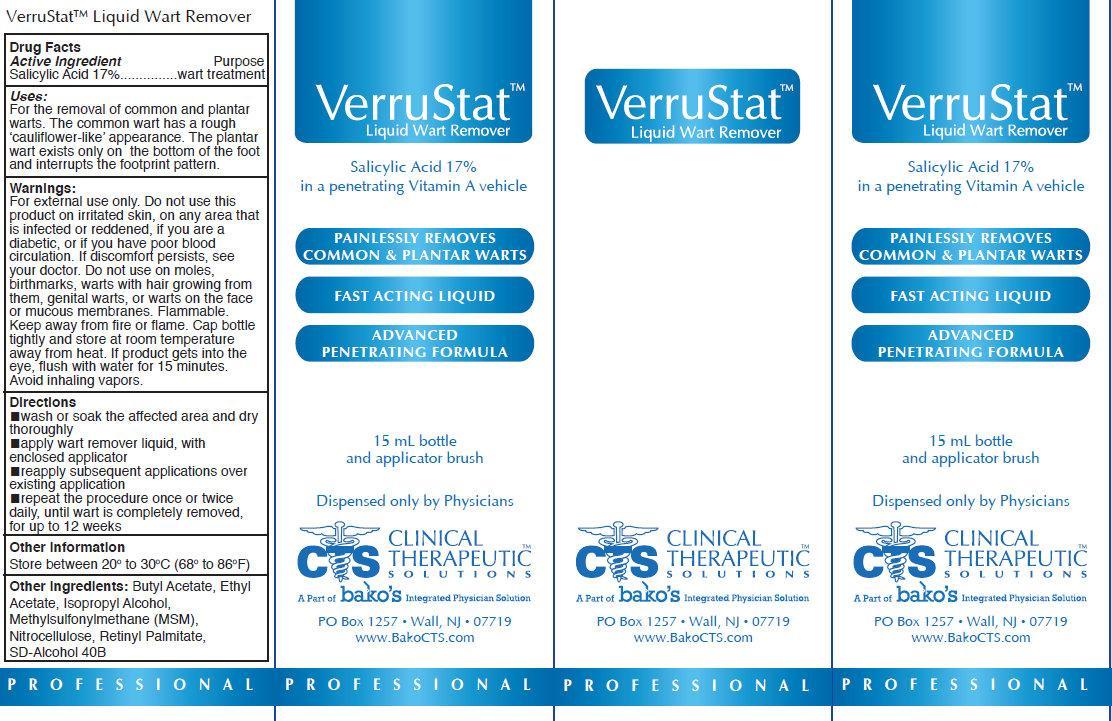 DRUG LABEL: VerruStat Wart Remover
NDC: 44577-020 | Form: LIQUID
Manufacturer: Clinical Therapeutic Solutions
Category: otc | Type: HUMAN OTC DRUG LABEL
Date: 20231105

ACTIVE INGREDIENTS: SALICYLIC ACID 170 mg/1 mL
INACTIVE INGREDIENTS: BUTYL ACETATE; ETHYL ACETATE; ISOPROPYL ALCOHOL; DIMETHYL SULFONE; PYROXYLIN; VITAMIN A PALMITATE; ALCOHOL

VerruStat Liquid Wart Remover

Active Ingredient

Salicylic Acid 17%

Purpose

wart treatment

Uses:

- For the removal of common and plantar warts. The common wart has a rough 'cauliflower-like' appearance. The plantar wart exists only on the bottom of the foot and interrupts the footprint pattern.

Warnings

For external use only. Do not use this product on irritated skin, on any area that is infected or reddened, if you are a diabetic, or if you have poor blood circulation. If discomfort persists, see your doctor. Do not use on moles, birthmarks, warts with hair growing from them, genital warts, or warts on the face or mucous membranes. Flammable. Keep away from fire or flame. Cap bottle tightly and store at room temperature away from heat. If product gets into the eye, flush with water for 15 minutes. Avoid inhaling vapors.

Directions

- wash or soak the affected area and dry thoroughly
- apply wart remover liquid, with enclosed applicator
- reapply subsequent applications over existing application
- repeat the procedure once or twice daily, until wart is completely removed, for up to 12 weeks

Other Information

- Store between 20 degrees to 30 degrees C (68 degrees to 86 degrees F)

Other Ingredients

Butyl Acetate, Ethyl Acetate, Isopropyl Alcohol, Methylsulfonylmethane (MSM), Nitrocellulose, Retinyl Palmitate, SD-Alcohol 40B